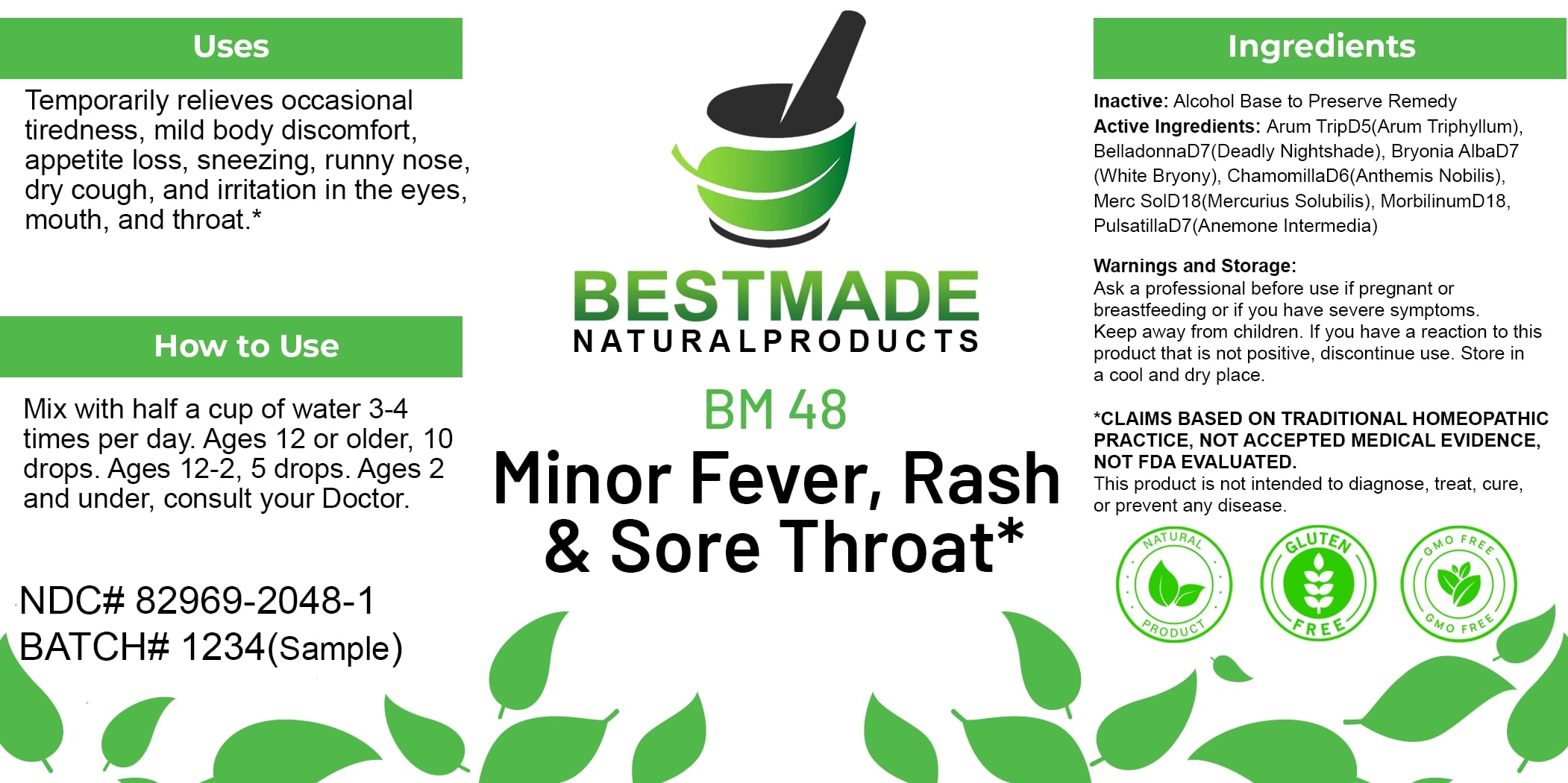 DRUG LABEL: Bestmade Natural Products BM48
NDC: 82969-2048 | Form: LIQUID
Manufacturer: Bestmade Natural Products
Category: homeopathic | Type: HUMAN OTC DRUG LABEL
Date: 20250123

ACTIVE INGREDIENTS: MERCURIUS SOLUBILIS 30 [hp_C]/30 [hp_C]; CHAMAEMELUM NOBILE 30 [hp_C]/30 [hp_C]; BRYONIA ALBA ROOT 30 [hp_C]/30 [hp_C]; MEASLES VIRUS 30 [hp_C]/30 [hp_C]; ATROPA BELLADONNA 30 [hp_C]/30 [hp_C]; ARISAEMA TRIPHYLLUM ROOT 30 [hp_C]/30 [hp_C]; PULSATILLA PRATENSIS 30 [hp_C]/30 [hp_C]
INACTIVE INGREDIENTS: ALCOHOL 30 [hp_C]/30 [hp_C]

BM48

DOSAGE AND ADMINISTRATION

How to Use

Mix with half a cup of water 3-4 times per day. Ages 12 or older, 10 drops. Ages 12-2, 5 drops. Ages 2 and under, consult your Doctor.

INACTIVE INGREDIENT

Ingredients

Inactive: Alcohol Base to Preserve Remedy

ACTIVE INGREDIENT

Active Ingredients: Arum Trip D5 (Arum Triphyllum), Belladonna D7 (Deadly Nightshade), Bryonia Alba D7 (White Bryony), Chamomilla D6 (Anthemis Nobilis), Merc Sol D18 (Mercurius Solubilis), Morbilinum D18, Pulsatilla D7 (Anemone Intermedia)

Uses

Temporarily relieves occasional tiredness, mild body discomfort, appetite loss, sneezing, runny nose, dry cough, and irritation in the eyes, mouth, and throat.*

*CLAIMS BASED ON TRADITIONAL HOMEOPATHIC PRACTICE, NOT ACCEPTED MEDICAL EVIDENCE, NOT FDA EVALUATED.

This product is not intended to diagnose, treat, cure, or prevent any disease.

Uses

Temporarily relieves occasional tiredness, mild body discomfort, appetite loss, sneezing, runny nose, dry cough, and irritation in the eyes, mouth, and throat.*

*CLAIMS BASED ON TRADITIONAL HOMEOPATHIC PRACTICE, NOT ACCEPTED MEDICAL EVIDENCE, NOT FDA EVALUATED.

This product is not intended to diagnose, treat, cure, or prevent any disease.

KEEP OUT OF REACH OF CHILDREN

Warnings and Storage:

Ask a professional before use if pregnant or breastfeeding or if you have severe symptoms. Keep away from children. If you have a reaction to this product that is not positive, discontinue use. Store in a cool and dry place.

Warnings and Storage:

Ask a professional before use if pregnant or breastfeeding or if you have severe symptoms. Keep away from children. If you have a reaction to this product that is not positive, discontinue use. Store in a cool and dry place.

*CLAIMS BASED ON TRADITIONAL HOMEOPATHIC PRACTICE, NOT ACCEPTED MEDICAL EVIDENCE, NOT FDA EVALUATED.

This product is not intended to diagnose, treat, cure, or prevent any disease.

Entire package label